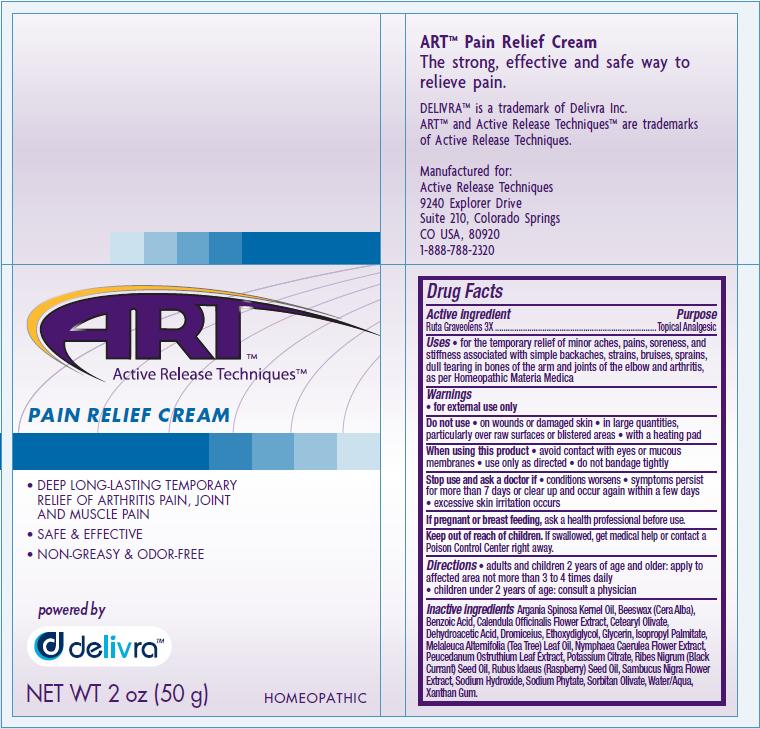 DRUG LABEL: Pain Relief 
NDC: 76029-001 | Form: CREAM
Manufacturer: Active Release Techniques LLC
Category: homeopathic | Type: HUMAN OTC DRUG LABEL
Date: 20110228

ACTIVE INGREDIENTS: RUTA GRAVEOLENS FLOWERING TOP 3 [hp_X]/50 g
INACTIVE INGREDIENTS: ARGAN OIL; YELLOW WAX; BENZOIC ACID; CALENDULA OFFICINALIS FLOWERING TOP; CETEARYL OLIVATE; DEHYDROACETIC ACID; DIETHYLENE GLYCOL MONOETHYL ETHER; GLYCERIN; ISOPROPYL PALMITATE; POTASSIUM CITRATE; RIBES NIGRUM SEED OIL; SAMBUCUS NIGRA FLOWER; SODIUM HYDROXIDE; SORBITAN OLIVATE; TEA TREE OIL; WATER; XANTHAN GUM

ACTIVE INGREDIENT

Ruta Graveolens 3X

PURPOSE

Topical Analgesic

INDICATIONS AND USAGE

for the temporary relief of minor aches, pains, soreness, and stiffness associated with simple backaches, strains, bruises, sprains, dull tearing in bones of the arm and joints of the elbow and arthritis, as per Homeopathic Materia Medica.

WARNINGS

for external use only

Do not use

- on wounds or damaged skin
- in large quantities particularly over raw surfaces or blistered areas
- with a heating pad

When using this product

- avoid contact with eyes or mucous membranes
- use only as directed
- do not bandage tightly

Stop use and ask a doctor if

- condition worsens
- symptoms persist for more than 7 days or clear up and occur again within a few days
- excessive skin irritation occurs

PREGNANCY OR BREAST FEEDING

If pregnant or breast feeding, ask a health professional before use.

Keep out of reach of children. If swallowed, get medical help or contact a Poison Control Center right away.

Directions

- adults and children 2 years of age and older: apply to affected are not more than 3 to 4 times daily
- children under 2 years of age: consult a physician

Inactive Ingredients

Argania Spinosa Kernel Oil, Beeswax (Cera Alba), Benzoic Acid, Calendula Officinalis Flower Extract, Cetearyl Olivate, Dehydroacetic Acid, Dromiceius, Ethoxydiglycol, Glycerin, Isopropyl Palmitate, Melaleuca Alternifolia (Tea Tree) Leaf Oil, Nymphaea Caerulea Flower Extract, Peucedanum Ostruthium Leaf Extract, Potassium Citrate, Ribes Nigrum (Black Currant) Seed Oil, Rubus Idaeus (Raspberry) Seed Oil, Sambucus Nigra Flower Extract, Sodium Hydroxide, Sodium Phytate, Sorbitan Olivate, Water/Aqua, Xanthan Gum

PACKAGE LABEL

Deep Long-Lasting Temporary Relief of Arthritis Pain, Joint and Muscle Pain

Safe and Effective

Non-Greasy and Odor Free